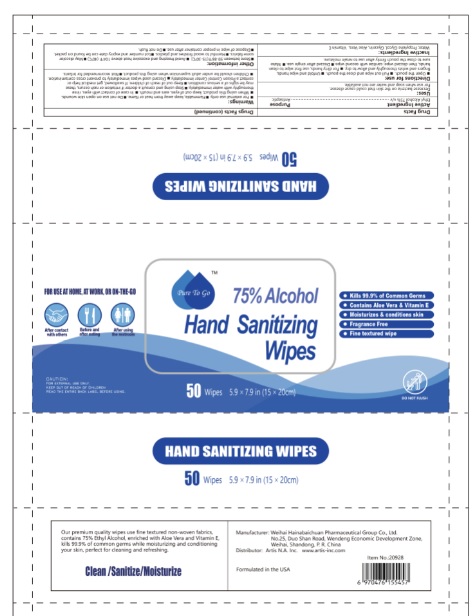 DRUG LABEL: Hand Sanitizing Wipes
NDC: 79798-001 | Form: CLOTH
Manufacturer: N A Artis Inc
Category: otc | Type: HUMAN OTC DRUG LABEL
Date: 20200706

ACTIVE INGREDIENTS: ALCOHOL 75 mL/100 mL
INACTIVE INGREDIENTS: .ALPHA.-TOCOPHEROL; ALOE; GLYCERIN; PROPYLENE GLYCOL; WATER

Active Ingredients

Ethyl Alcohol 75% v/v.

Purpose

Antiseptic

Warnings

For external use only.

Flammable, keep away from heat or flame.

Do not use

- on open skin wounds.

When using this product, keep out of eyes, ears and mouth. In case of contact with eyes,rinse thoroughly with water immediately.

Stop using and consult a doctor if irritation or rash occurs, these may be sighs of a serious condition.

- Discard used wipes immediately to prevent cross contamination.
- Children should be under adult supervision when using this product.
- Not recommended for infants.

Keep out of reach of children.

If swallowed, get medical help or contact a Poison Control Center immediately.

Uses

- Decrease bacteria on the skin that could cause disease.
- For use when soap and water are not available.

Directions

- Open the pouch.
- Pull out wipe and close the pouch.
- Unfold and wipe hands, fingers and wrists thoroughly and allow to dry.
- For dirty hands, use first wipe to clean hands, then discard wipe; sanitize with second wipe.
- Discard after single use.
- Make sure to close the pouch firmly after use to retain moisture.

Other Information

- Store between 59-86℉(15-30℃)
- Avoid freezing and excessive heat above 104℉ (40℃)
- May discolor some fabrics.
- Harmful to wood finishes and plastics.
- Lot number and expiry date can be found on packet.
- Dispose of wipe in proper container after use.
- Do not flush.

Inactive Ingredients

Water, Propylene Glycol, Glycerin, Aloe Vera, Vitamin E